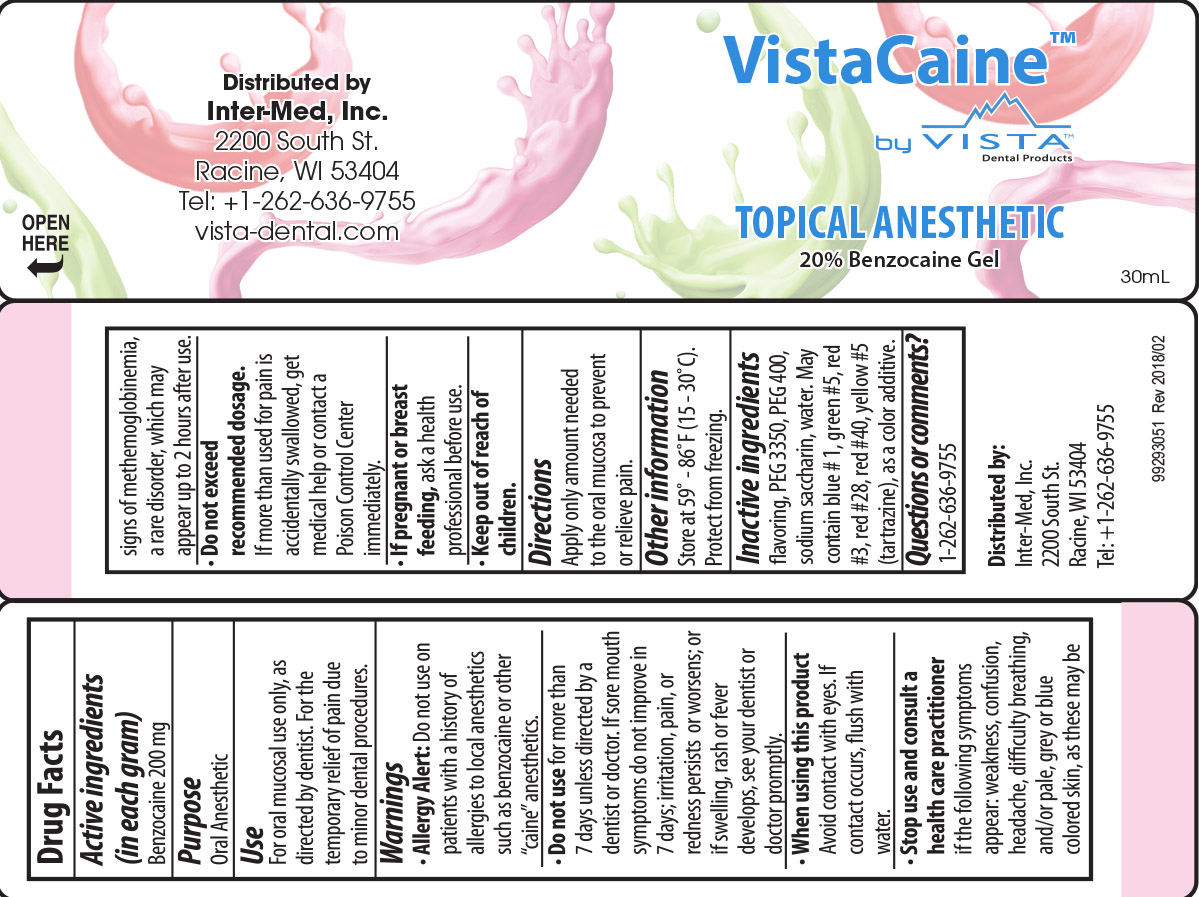 DRUG LABEL: VistaCaine Topical Anesthetic
NDC: 64522-003 | Form: GEL
Manufacturer: Inter-Med, INC.
Category: otc | Type: HUMAN OTC DRUG LABEL
Date: 20220124

ACTIVE INGREDIENTS: BENZOCAINE 200 mg/1 g
INACTIVE INGREDIENTS: POLYETHYLENE GLYCOL 3350; POLYETHYLENE GLYCOL 400; SACCHARIN SODIUM; WATER; FD&C BLUE NO. 1; D&C GREEN NO. 5; FD&C RED NO. 3; D&C RED NO. 28; FD&C YELLOW NO. 5; FD&C RED NO. 40

Active Ingredients (in each gram)

Benzocaine 200 mg

Purpose

Oral Anesthetic

Use

For oral mucosal use only, as directed by dentist. For the temporary relief of pain due to minor dental procedures.

Warnings

- Allergy Alert: Do not use on patients with a history of allergies to local anesthetics such as benzocaine or other "caine" anesthetics.
- Do Not Use for more than 7 days unless directed by a dentist or doctor. If sore mouth symptoms do not improve in 7 days; irritation, pain or redness persists or worsens; or if swelling, rash or fever develops, see your dentist or doctor promptly.
- When using this product avoid contact with eyes. If contact occurs, flush with water.
- Stop use and consult a health care practitioner if the following symptoms appear: weakness, confusion, headache, difficulty breathing, and/or pale, grey or blue colored skin, as these may be signs of methemoglobinemia, a rare disorder, which may appear up to 2 hours after use.
- Do not exceed recommended dosage. If more than used for pain is accidentally swallowed, get medical help or contact a Poison Control Center immediately.
- If pregnant or breast feeding, ask a health professional before use.

Keep Out of Reach of Children.

Directions

Apply only amount needed to the oral mucosa to prevent or relieve pain.

Other Information

Store at 59º -86°F (15 - 30°C).

Protect from freezing.

Inactive ingredients

flavoring, PEG 3350, PEG 400, sodium saccharin, water. May contain blue #1, green #5, red #3, red #28, red #40, yellow #5 (tartrazine), as a color additive.

Questions or comments?

1-262-636-9755